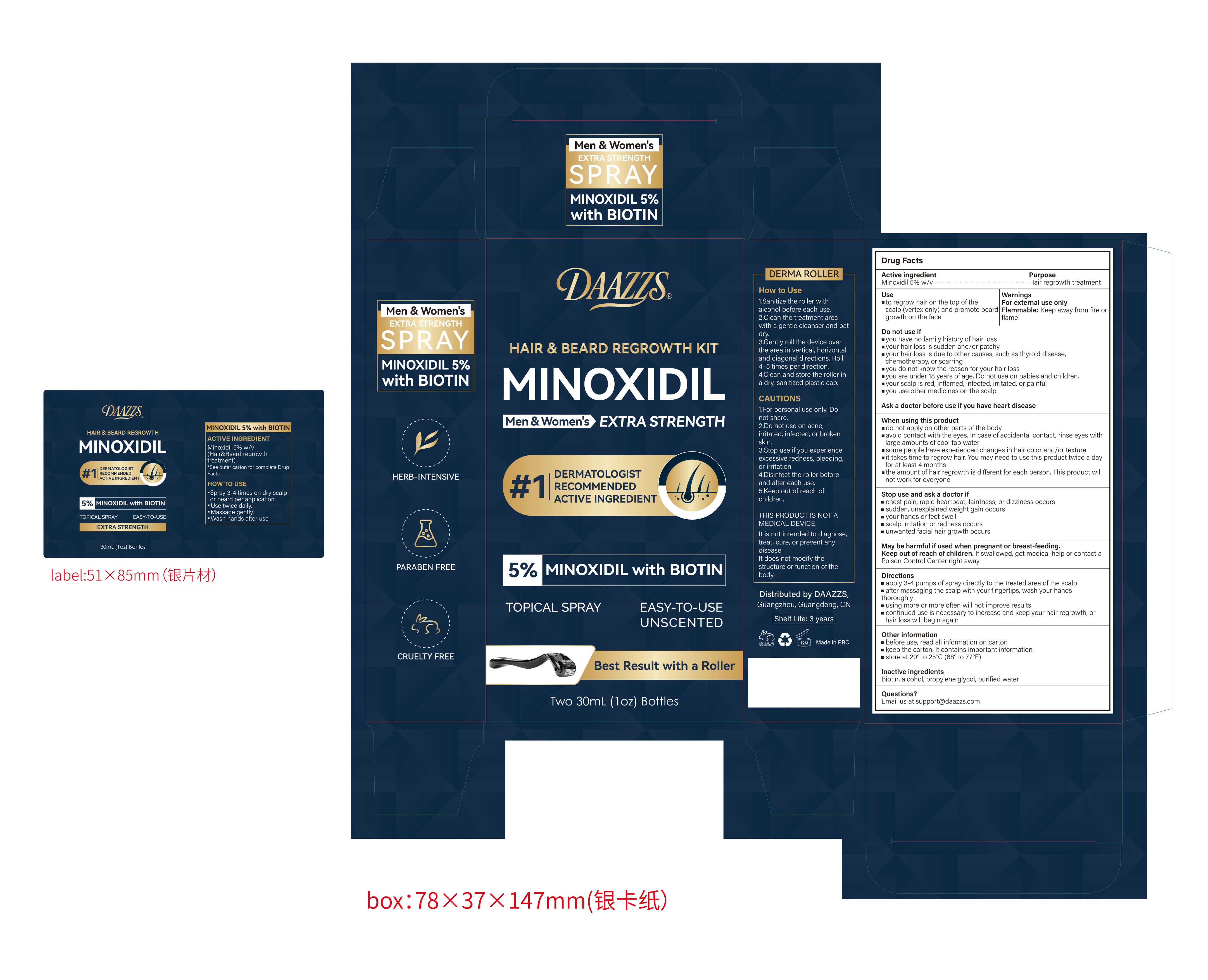 DRUG LABEL: DAAZZS 5% Minoxidil Hair and Beard Regrowth Kit with Biotin
NDC: 87408-008 | Form: SPRAY
Manufacturer: Guangzhou Jingliang Cosmetics Co., Ltd.
Category: otc | Type: HUMAN OTC DRUG LABEL
Date: 20260218

ACTIVE INGREDIENTS: MINOXIDIL 5 g/100 mL
INACTIVE INGREDIENTS: WATER; BIOTIN; ALCOHOL; PROPYLENE GLYCOL

Active Ingredient

Minoxidil 5% w/v

Ask a doctore before use

Ask a doctor before use if you have heart disease

Keep Oot Of Reach Of Children

Keep out of reach of children. If swallowed, get medical help or contact a Poison Control Center right away

Purpose

Hair regrowth treatment

Stop Use

Stop use and ask a doctor if

- chest pain, rapid heartbeat, faintness, or dizziness occurs

- sudden, unexplained weight gain occurs

- your hands or feet swell

- scalp irritation or redness occurs

- unwanted facial hair growth occurs

When Using

- do not apply on other parts of the body

- avoid contact with the eyes. In case of accidental contact, rinse eyes with

large amounts of cool tap water

- some people have experienced changes in hair color and/or texture

- it takes time to regrow hair. You may need to use this product twice a day

for at least 4 months

- the amount of hair regrowth is different for each person. This product will

not work for everyone

Inactive ingredients

Biotin, alcohol, propylene glycol, purified water

Directions

- apply 3-4 pumps of spray directly to the treated area of the scalp

- after massaging the scalp with your fingertips, wash your hands thoroughly

- using more or more often will not improve results

- continued use is necessary to increase and keep your hair regrowth, or hair loss will begin again

Warnings

For external use only.

Uses

- to regrow hair on the top of the scalp (vertex only) and promote beard growth on the face

Do Not Use

- you have no family history of hair loss

- your hair loss is sudden and/or patchy

- your hair loss is due to other causes, such as thyroid disease,

chemotherapy, or scarring

- you do not know the reason for your hair loss

- you are under 18 years of age. Do not use on babies and children.

- your scalp is red, inflamed, infected, irritated, or painful

- you use other medicines on the scalp

PACKAGE LABEL

Brand: DAAZZS

Name: 5% MINOXIDIL with BIOTIN HAIR & BEARD REGROWTH KIT with Biotin

Size: 30 ML x 2 Bottles